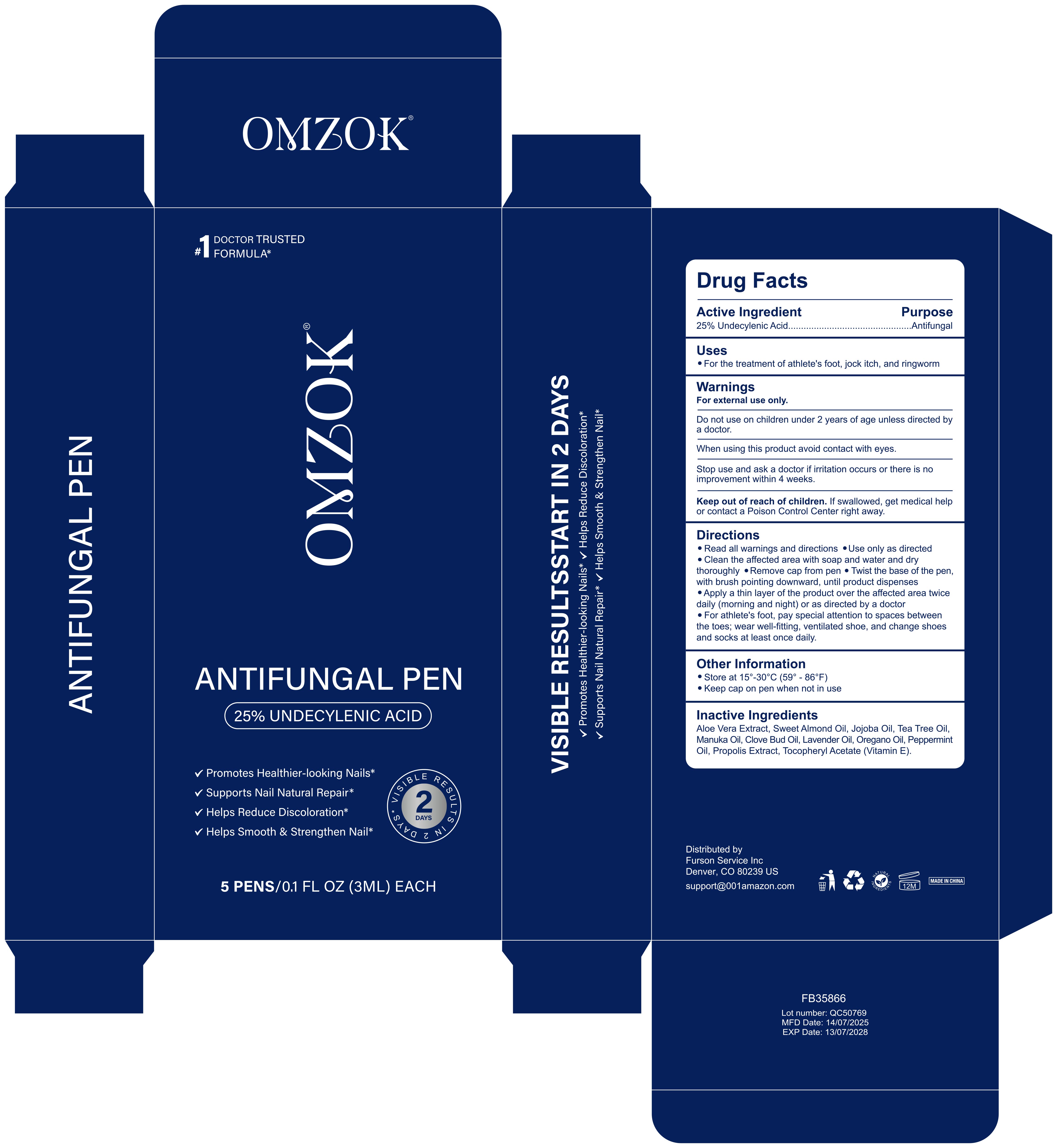 DRUG LABEL: OMZOK ANTIFUNGAL PEN
NDC: 83804-007 | Form: LIQUID
Manufacturer: Shenzhen Shandian Jingling Technology Co., Ltd.
Category: otc | Type: HUMAN OTC DRUG LABEL
Date: 20250702

ACTIVE INGREDIENTS: UNDECYLENIC ACID 25 g/100 mL
INACTIVE INGREDIENTS: TEA TREE OIL; MANUKA OIL; LAVENDER OIL; OREGANO LEAF OIL; ALPHA-TOCOPHEROL ACETATE; JOJOBA OIL; PROPOLIS WAX; CLOVE OIL; ALMOND OIL; ALOE VERA LEAF; PEPPERMINT OIL

83804-007 OMZOK ANTIFUNGAL PEN

ACTIVE INGREDIENT

UNDECYLENIC ACID 25%

PURPOSE

Antifungal

INDICATIONS AND USAGE

For the treatment of athlete's foot, jock itch, and ringworm

WARNINGS

For external use only.

Do not use on children under 2 years of age unless directed bya doctor.

When using this product avoid contact with eyes

Stop use and ask a doctor if irritation occurs or there is noimprovement within 4 weeks

Keep out of reach of children. lf swallowed, get medical helpor contact a Poison Control Center right away

DOSAGE AND ADMINISTRATION

Read all warnings and directions oUse only as directed
Clean the affected area with soap and water and drythoroughly
Remove cap from pen e Twist the base of the pen,with brush pointing downward, until product dispenses
Apply a thin layer of the product over the affected area twicedaily (morning and night) or as directed by a doctor
For athlete's foot, pay special attention to spaces betweenthe toes; wear well-fitting, ventilated shoe, and change shoesand socks at least once daily.

INACTIVE INGREDIENT

ALOE VERA LEAF
SWEET ALMOND OIL
JOJOBA OIL
TEA TREE OIL
MANUKA OIL
CLOVE BUD OIL
LAVENDER OIL
OREGANO OIL
PEPPERMINT OIL
PROPOLIS WAX
ALPHA.-TOCOPHEROL ACETATE (vitamin E)